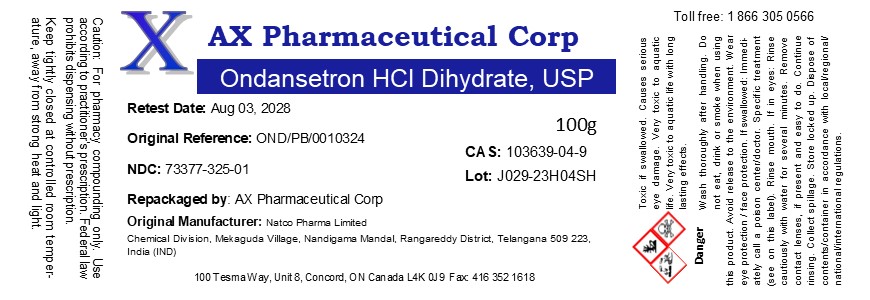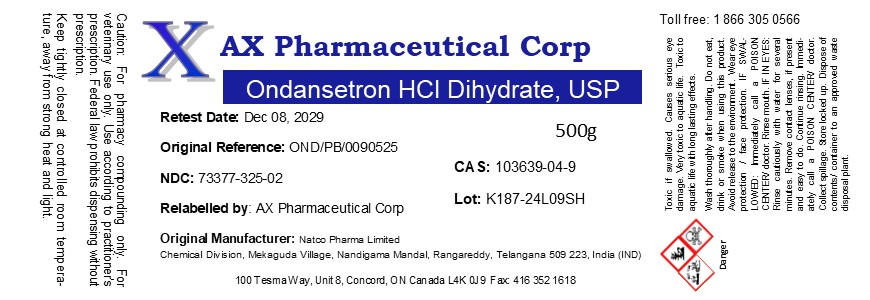 DRUG LABEL: Ondansetron HCl Dihydrate
NDC: 73377-325 | Form: POWDER
Manufacturer: AX Pharmaceutical Corp
Category: other | Type: BULK INGREDIENT - ANIMAL DRUG
Date: 20250917

ACTIVE INGREDIENTS: ONDANSETRON HYDROCHLORIDE 1 g/1 g

Ondansetron HCl Dihydrate